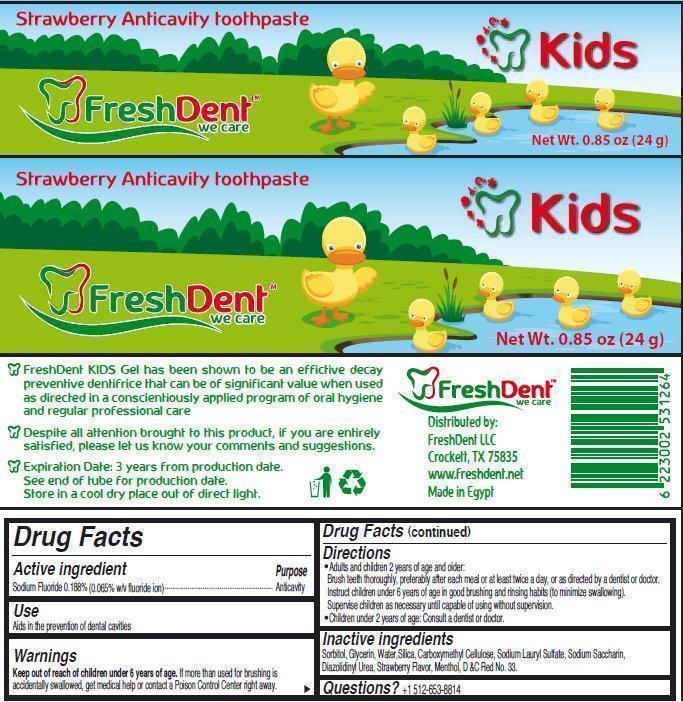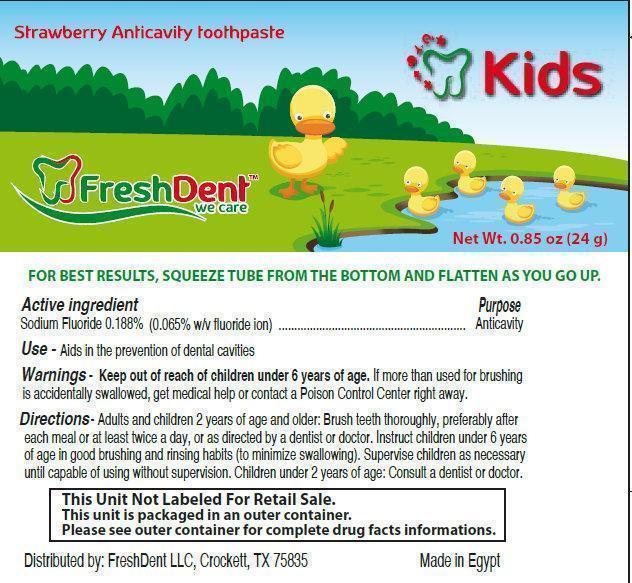 DRUG LABEL: FreshDent Kids Strawberry Anticavity Tooth
NDC: 69338-001 | Form: PASTE, DENTIFRICE
Manufacturer: FreshDent LLC
Category: otc | Type: HUMAN OTC DRUG LABEL
Date: 20141106

ACTIVE INGREDIENTS: SODIUM FLUORIDE 0.65 mg/1 g
INACTIVE INGREDIENTS: SORBITOL; GLYCERIN; WATER; SILICON DIOXIDE; CARBOXYMETHYLCELLULOSE; SODIUM LAURYL SULFATE; SACCHARIN SODIUM; DIAZOLIDINYL UREA; MENTHOL; D&C RED NO. 33

FreshDent Kids Strawberry Anticavity Toothpaste

Active Ingredients

Sodium Fluoride 0.188% (0.065% w/v fluoride ion)

Purpose

Anticavity

Keep out of reach of children under 6 years of age. If more than used for brushing is accidentally swallowed, get medical help or contact a Poison Control Center right away.

Directions

- Adults and children 2 years of age and older: Brush teeth thoroughly, preferably after each meal or at least twice a day, or as directed by a dentist or doctor. Instruct children under 6 years of age in good brushing and rinsing habits (to minimize swallowing). Supervise children as necessary until capable of using without supervision.

- Children under 2 years of age: Consult a dentist or doctor.

Inactive Ingredients

Sorbitol, Glycerin, Water,Silica, Carboxymethyl Cellulose, Lauryl Sulfate, Sodium Saccharin, Diazolidinyl Urea, Strawberry Flavor, Menthol, D &C Red No. 33.

Questions?

+1-512-653-8814

Package Label

Strawberry Anticavity toothpaste

FreshDent Kids

we care

Net Wt. 0.85 oz (24 g)

Distributed by: FreshDent LLC Crockett, TX 75835 www.freshdent.net Made in Egypt